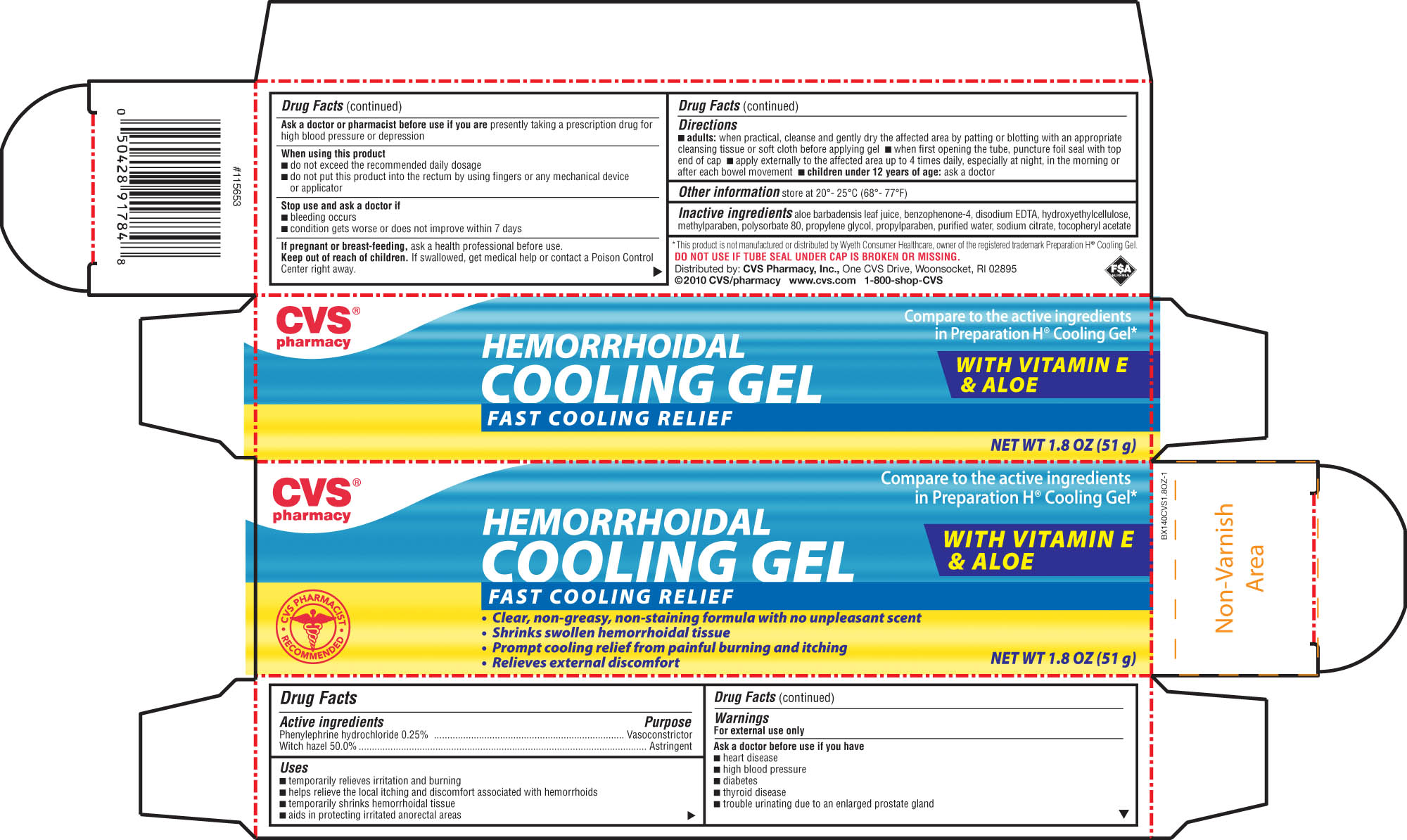 DRUG LABEL: CVS HEMORRHOIDAL COOLING 
NDC: 59779-265 | Form: GEL
Manufacturer: CVS Pharmacy
Category: otc | Type: HUMAN OTC DRUG LABEL
Date: 20101118

ACTIVE INGREDIENTS: WITCH HAZEL 500 mg/1 g; PHENYLEPHRINE HYDROCHLORIDE 2.5 mg/1 g
INACTIVE INGREDIENTS: WATER; SULISOBENZONE; PROPYLENE GLYCOL; POLYSORBATE 80; ALPHA-TOCOPHEROL; ALOE VERA LEAF; ANHYDROUS TRISODIUM CITRATE; EDETATE DISODIUM; HYDROXYETHYL CELLULOSE (4000 MPA.S FOR 1% AQUEOUS SOLUTION); METHYLPARABEN; PROPYLPARABEN

drug facts

Active ingredients Purpose
Phenylephrine hydrochloride 0.25%.............................Vasoconstrictor
Witch hazel 50.0%.....................................................Astringent

Uses
- temporarily relieves irritation and burning
- helps relieve the local itching and discomfort associated with hemorrhoids
- temporarily shrinks hemorrhoidal tissue
- aids in protecting irritated anorectal areas

Keep out of reach of children. If swallowed, get medical help or contact
a Poison Control Center right away.

Uses
- temporarily relieves irritation and burning
- helps relieve the local itching and discomfort associated with hemorrhoids
- temporarily shrinks hemorrhoidal tissue
- aids in protecting irritated anorectal areas
Other information- store at 20 degrees - 25 degrees C (68 degrees - 77 degrees F)

Warnings
For external use only.
Ask a doctor before use if you have
- heart disease - high blood pressure - thyroid disease - diabetes
- trouble urinating due to an enlarged prostate gland
Ask a doctor before use if you have
- heart disease
- high blood pressure
- diabetes
- thyroid disease
- trouble urinating due to an enlarged prostate gland
Ask a doctor or pharmacist before use if you are presently taking
a prescription drug for high blood pressure or depression
When using this product
- do not exceed the recommended daily dosage
- do not put into rectum by using fingers or any mechanical device or applicator
Stop use and ask a doctor if
- bleeding occurs
- condition worsens or does not improve within 7 days
If pregnant or breast feeding, ask a health professional before use.
Keep out of the reach of children.If swallowed, get medical help or contact a Poison Control Center right away

Directions
- adults: when practical, cleanse and gently dry the affected area by patting or blotting with an
appropriate cleansing tissue or soft cloth before applying gel
- when first opening the tube, puncture foil seal with top end of cap
- apply externally to the affected area up to 4 times daily, especially at night,
in the morning or after each bowel movement
- children under 12 years of age: ask a doctor

INACTIVE INGREDIENT

Inactive Ingredients aloe barbadensis leaf juice, benzophenone-4, disodium EDTA,
hydroxyethylcellulose. methyl paraben, polysorbate 80, propylene glycol, propylparaben,
purified water, sodium citrate, tocopheryl acetate